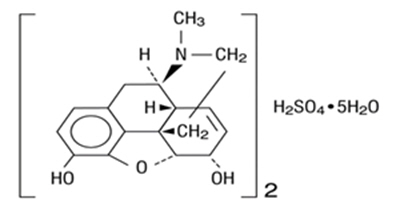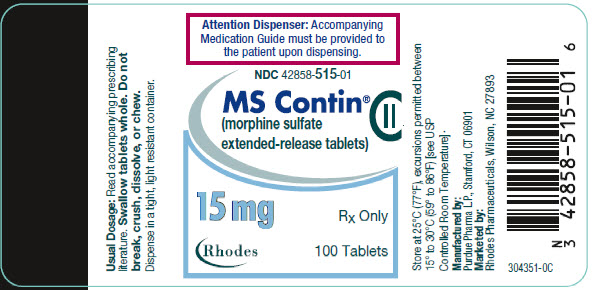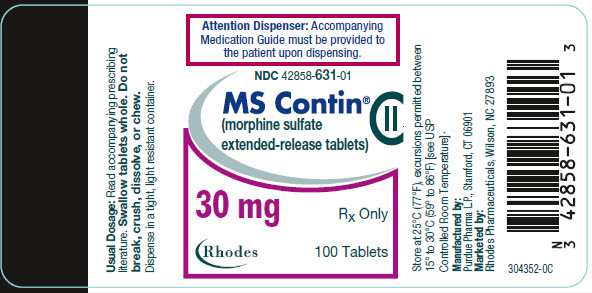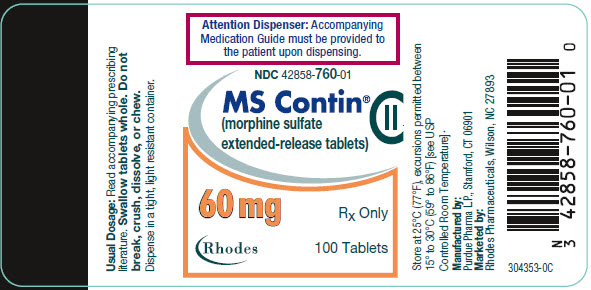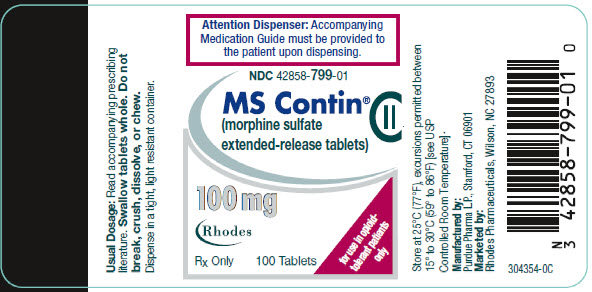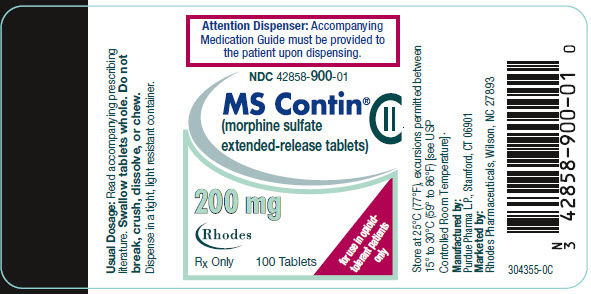 DRUG LABEL: MS Contin
NDC: 42858-515 | Form: TABLET
Manufacturer: Rhodes Pharmaceuticals L.P.
Category: prescription | Type: HUMAN PRESCRIPTION DRUG LABEL
Date: 20260102
DEA Schedule: CII

ACTIVE INGREDIENTS: morphine sulfate 15 mg/1 1
INACTIVE INGREDIENTS: cetostearyl alcohol; hydroxyethyl cellulose (140 MPA.S at 5%); hypromellose, unspecified; magnesium stearate; polyethylene glycol, unspecified; talc; titanium dioxide; FD&C Blue No. 2; lactose, unspecified form; polysorbate 80

HIGHLIGHTS OF PRESCRIBING INFORMATION

These highlights do not include all the information needed to use MS CONTIN® safely and effectively. See full prescribing information for MS CONTIN.
MS CONTIN® (morphine sulfate extended-release tablets), for oral use CII
Initial U.S. Approval: 1941

WARNING: SERIOUS AND LIFE-THREATENING RISKS FROM USE OF MS CONTIN

See full prescribing information for complete boxed warning.

- MS CONTIN exposes users to risks of addiction, abuse, and misuse, which can lead to overdose and death. Assess patient's risk before prescribing and reassess regularly for these behaviors and conditions. (5.1)
- Serious, life-threatening, or fatal respiratory depression may occur, especially during initiation or following a dosage increase. To reduce the risk of respiratory depression, proper dosing and titration of MS CONTIN are essential. Instruct patients to swallow MS CONTIN tablets whole to avoid exposure to a potentially fatal dose of morphine. (5.2)
- Accidental ingestion of MS CONTIN, especially by children, can result in a fatal overdose of morphine. (5.2)
- Concomitant use of opioids with benzodiazepines or other central nervous system (CNS) depressants, including alcohol, may result in profound sedation, respiratory depression, coma, and death. Reserve concomitant prescribing for use in patients for whom alternative treatment options are inadequate. (5.3, 7)
- Advise pregnant women using opioids for an extended period of time of the risk of Neonatal Opioid Withdrawal Syndrome, which may be life-threatening if not recognized and treated. Ensure that management by neonatology experts will be available at delivery. (5.4)
- Healthcare providers are strongly encouraged to complete a REMS compliant education program and to counsel patients and caregivers on serious risks, safe use, and the importance of reading the Medication Guide with each prescription. (5.5)

RECENT MAJOR CHANGES

Boxed Warning | 12/2025
Indications and Usage (1) | 12/2025
Dosage and Administration (2.2, 2.3, 2.6) | 12/2025
Warnings and Precautions (5.1, 5.2, 5.3, 5.12, 5.14) | 12/2025

1 INDICATIONS AND USAGE

MS CONTIN is an opioid agonist indicated for the management of severe and persistent pain that requires an opioid analgesic and that cannot be adequately treated with alternative options, including immediate-release opioids. (1)

Limitations of Use

- Because of the risks of addiction, abuse, misuse, overdose, and death, which can occur at any dosage or duration and persist over the course of therapy, reserve opioid analgesics, including MS CONTIN, for use in patients for whom alternative treatment options are ineffective, not tolerated, or would be otherwise inadequate to provide sufficient management of pain. (1, 5.1)
- MS CONTIN is not indicated as an as-needed (prn) analgesic. (1)

2 DOSAGE AND ADMINISTRATION

- MS CONTIN should be prescribed only by healthcare providers who are knowledgeable about the use of extended-release/long-acting opioids and how to mitigate the associated risks. (2.1)
- MS CONTIN 100 mg and 200 mg tablets, a single dose greater than 60 mg, or a total daily dose greater than 120 mg, are only for use in patients in whom tolerance to an opioid of comparable potency has been established. (2.1)
- Patients considered opioid-tolerant are those taking, for one week or longer, at least 60 mg of morphine per day, 25 mcg transdermal fentanyl per hour, 30 mg of oral oxycodone per day, 8 mg of oral hydromorphone per day, 25 mg oral oxymorphone per day, 60 mg oral hydrocodone per day, or an equianalgesic dose of another opioid. (2.1)
- Use the lowest effective dosage for the shortest duration of time consistent with individual patient treatment goals. Reserve titration to higher doses of MS CONTIN for patients in whom lower doses are insufficiently effective and in whom the expected benefits of using a higher dose opioid clearly outweigh the substantial risks. (2.1, 5)
- Initiate the dosing regimen for each patient individually, taking into account the patient's underlying cause and severity of pain, prior analgesic treatment and response, and risk factors for addiction, abuse, and misuse. (2.1, 5.1)
- Respiratory depression can occur at any time during opioid therapy, especially when initiating and following dosage increases with MS CONTIN. Consider this risk when selecting an initial dose and when making dose adjustments. (2.1, 5.2)
- Instruct patients to swallow MS CONTIN tablets intact and not to cut, break, chew, crush, or dissolve MS CONTIN (risk of potentially fatal dose). (2.1, 5.1)
- Discuss opioid overdose reversal agents and options for acquiring them with the patient and/or caregiver, both when initiating and renewing treatment with MS CONTIN, especially if the patient has additional risk factors for overdose, or close contacts at risk for exposure and overdose. (2.2, 5.1, 5.2, 5.3)
- MS CONTIN is administered orally once every 8 or 12 hours. (2.3)
- For patients who are not opioid tolerant, initiate with 15 mg tablets orally every 8 to 12 hours. (2.3)
- Periodically reassess patients receiving MS CONTIN to evaluate the continued need for opioid analgesics to maintain pain control, for the signs or symptoms of adverse reactions, and for the development of addiction, abuse, or misuse. (2.4)
- Do not rapidly reduce or abruptly discontinue MS CONTIN in a physically dependent patient because rapid reduction or abrupt discontinuation of opioid analgesics has resulted in serious withdrawal symptoms, uncontrolled pain, and suicide. (2.5, 5.14)

3 DOSAGE FORMS AND STRENGTHS

Extended-release tablets: 15 mg, 30 mg, 60 mg, 100 mg, 200 mg (3)

4 CONTRAINDICATIONS

- Significant respiratory depression (4)
- Acute or severe bronchial asthma in an unmonitored setting or in the absence of resuscitative equipment (4)
- Concurrent use of monoamine oxidase inhibitors (MAOIs) or use of MAOIs within the last 14 days (4)
- Known or suspected gastrointestinal obstruction, including paralytic ileus (4)
- Hypersensitivity to morphine (4)

5 WARNINGS AND PRECAUTIONS

- Opioid-Induced Hyperalgesia and Allodynia: Opioid-Induced Hyperalgesia (OIH) occurs when an opioid analgesic paradoxically causes an increase in pain, or an increase in sensitivity to pain. If OIH is suspected, carefully consider appropriately decreasing the dose of the current opioid analgesic, or opioid rotation. (5.6)
- Life-Threatening Respiratory Depression in Patients with Chronic Pulmonary Disease or in Elderly, Cachectic, or Debilitated Patients: Regularly evaluate, particularly during initiation and titration. (5.7)
- Adrenal Insufficiency: If diagnosed, treat with physiologic replacement of corticosteroids, and wean patient off of the opioid. (5.9)
- Severe Hypotension: Regularly evaluate during dosage initiation and titration. Avoid use in patients with circulatory shock. (5.10)
- Risks of Use in Patients with Increased Intracranial Pressure, Brain Tumors, Head Injury, or Impaired Consciousness: Monitor for sedation and respiratory depression. Avoid use of MS CONTIN in patients with impaired consciousness or coma. (5.11)

6 ADVERSE REACTIONS

Most common adverse reactions (>10%): constipation, nausea, and sedation. (6.1)

To report SUSPECTED ADVERSE REACTIONS, contact Rhodes Pharmaceuticals at 1-888-827-0616 or FDA at 1-800-FDA-1088 or www.fda.gov/medwatch

7 DRUG INTERACTIONS

- Serotonergic Drugs: Concomitant use may result in serotonin syndrome. Discontinue MS CONTIN if serotonin syndrome is suspected. (7)
- Mixed Agonist/Antagonist and Partial Agonist Opioid Analgesics: Avoid use with MS CONTIN because they may reduce analgesic effect of MS CONTIN or precipitate withdrawal symptoms. (5.14, 7)

8 USE IN SPECIFIC POPULATIONS

- Pregnancy: May cause fetal harm. (8.1)
- Lactation: Not recommended. (8.2)

FULL PRESCRIBING INFORMATION

WARNING: SERIOUS AND LIFE-THREATENING RISKS FROM USE OF MS CONTIN

Addiction, Abuse, and Misuse

Because the use of MS CONTIN exposes patients and other users to the risks of opioid addiction, abuse, and misuse, which can lead to overdose and death, assess each patient's risk prior to prescribing and reassess all patients regularly for the development of these behaviors and conditions [see Warning and Precautions (5.1)].

Life-Threatening Respiratory Depression

Serious, life-threatening, or fatal respiratory depression may occur with use of MS CONTIN, especially during initiation or following a dosage increase. To reduce the risk of respiratory depression, proper dosing and titration of MS CONTIN are essential. Instruct patients to swallow MS CONTIN tablets whole; crushing, chewing, or dissolving MS CONTIN tablets can cause rapid release and absorption of a potentially fatal dose of morphine. [see Warnings and Precautions (5.2)].

Accidental Ingestion

Accidental ingestion of even one dose of MS CONTIN, especially by children, can result in a fatal overdose of morphine [see Warnings and Precautions (5.2)].

Risks From Concomitant Use With Benzodiazepines Or Other CNS Depressants

Concomitant use of opioids with benzodiazepines or other central nervous system (CNS) depressants, including alcohol, may result in profound sedation, respiratory depression, coma, and death. Reserve concomitant prescribing of MS CONTIN and benzodiazepines or other CNS depressants for use in patients for whom alternative treatment options are inadequate [see Warnings and Precautions (5.3), Drug Interactions (7)].

Neonatal Opioid Withdrawal Syndrome (NOWS)

Advise pregnant women using opioids for an extended period of time of the risk of Neonatal Opioid Withdrawal Syndrome, which may be life-threatening if not recognized and treated. Ensure that management by neonatology experts will be available at delivery [see Warnings and Precautions (5.4)].

Opioid Analgesic Risk Evaluation and Mitigation Strategy (REMS)

Healthcare providers are strongly encouraged to complete a REMS-compliant education program, and to counsel patients and caregivers on serious risks, safe use, and the importance of reading the Medication Guide with each prescription [see Warning and Precautions (5.5)].

1 INDICATIONS AND USAGE

MS CONTIN is indicated for the management of severe and persistent pain that requires an opioid analgesic and that cannot be adequately treated with alternative options, including immediate-release opioids.

Limitations of Use

- Because of the risks of addiction, abuse, misuse, overdose, and death, which can occur at any dosage or duration and persist over the course of therapy [see Warnings and Precautions (5.2)], reserve opioid analgesics, including MS CONTIN, for use in patients for whom alternative treatment options are ineffective, not tolerated, or would be otherwise inadequate to provide sufficient management of pain.
- MS CONTIN is not indicated as an as-needed (prn) analgesic.

2 DOSAGE AND ADMINISTRATION

2.1 Important Dosage and Administration Instructions

- MS CONTIN should be prescribed by healthcare professionals who are knowledgeable about the use of extended-release/long-acting opioids and how to mitigate the associated risks.
- MS CONTIN 100 mg and 200 mg tablets, a single dose greater than 60 mg, or a total daily dose greater than 120 mg, are only for use in patients in whom tolerance to an opioid of comparable potency has been established. Patients considered opioid-tolerant are those taking, for one week or longer, at least 60 mg morphine per day, 25 mcg transdermal fentanyl per hour, 30 mg oral oxycodone per day, 8 mg oral hydromorphone daily, 25 mg oral oxymorphone per day, 60 mg oral hydrocodone per day, or an equianalgesic dose of another opioid.
- Use the lowest effective dosage for the shortest duration of time consistent with individual patient treatment goals [see Warnings and Precautions (5)]. Because the risk of overdose increases as opioid doses increase, reserve titration to higher doses of MS CONTIN for patients in whom lower doses are insufficiently effective and in whom the expected benefits of using a higher dose opioid clearly outweigh the substantial risks.
- Initiate the dosing regimen for each patient individually, taking into account the patient's underlying cause and severity of pain, prior analgesic treatment and response, and risk factors for addiction, abuse, and misuse [see Warnings and Precautions (5.1)].
- Respiratory depression can occur at any time during opioid therapy, especially when initiating and following dosage increases with MS CONTIN. Consider this risk when selecting an initial dose and when making dose adjustments [see Warning and Precautions (5.2)].
- MS CONTIN is administered orally once every 8 or 12 hours.
- Instruct patients to swallow MS CONTIN tablets whole. Crushing, chewing, or dissolving MS CONTIN tablets will result in uncontrolled delivery of morphine and can lead to overdose or death [see Warnings and Precautions (5.1)].

2.2 Patient Access to an Opioid Overdose Reversal Agent for the Emergency Treatment of Opioid Overdose

Inform patients and caregivers about opioid overdose reversal agents (e.g., naloxone, nalmefene). Discuss the importance of having access to an opioid overdose reversal agent, especially if the patient has risk factors for overdose (e.g., concomitant use of CNS depressants, a history of opioid use disorder, or prior opioid overdose) or if there are household members (including children) or other close contacts at risk for accidental ingestion or opioid overdose. The presence of risk factors for overdose should not prevent the management of pain in any patient [see Warnings and Precautions (5.1, 5.2, 5.3)].

Discuss the options for obtaining an opioid overdose reversal agent (e.g., prescription, over-the-counter, or as part of a community-based program) [see Warnings and Precautions (5.2)].

There are important differences among the opioid overdose reversal agents, such as route of administration, product strength, approved patient age range, and pharmacokinetics. Be familiar with these differences, as outlined in the approved labeling for those products, prior to recommending or prescribing such an agent.

2.3 Initial Dosage

It is safer to underestimate a patient's 24-hour oral morphine dosage and provide rescue medication (e.g., immediate-release opioid) than to overestimate the 24-hour oral morphine dosage and manage an adverse reaction due to an overdose. While useful tables of opioid equivalents are readily available, there is inter-patient variability in the potency of opioid drugs and opioid formulations. Frequently reevaluate patients for signs and symptoms of opioid withdrawal and for signs of oversedation/toxicity after converting patients to MS CONTIN.

Use of MS CONTIN in Patients who are not Opioid Tolerant

The starting dose for patients who are not opioid tolerant is MS CONTIN 15 mg orally every 8 to 12 hours. Use of higher starting doses in patients who are not opioid tolerant may cause fatal respiratory depression [see Warnings and Precautions (5.2)].

Conversion from Other Oral Morphine Formulations to MS CONTIN

Patients receiving other oral morphine formulations may be converted to MS CONTIN by administering one-half of the patient's 24-hour requirement as MS CONTIN on an every-12-hour schedule or by administering one-third of the patient's daily requirement as MS CONTIN on an every-8-hour schedule.

Conversion from Parenteral Morphine or Other Parenteral Opioid Analgesics to MS CONTIN

When converting from parenteral morphine or other parenteral non-morphine opioids to MS CONTIN, consider the following general points:

Parenteral to oral morphine ratio:

Between 2 to 6 mg of oral morphine may be required to provide analgesia equivalent to 1 mg of parenteral morphine. Typically, a dose of morphine that is approximately three times the previous daily parenteral morphine requirement is sufficient.

Other parenteral non-morphine opioid analgesics to oral morphine ratios:

Specific recommendations are not available because of a lack of systematic evidence for these types of analgesic substitutions. Published relative potency data are available, but such ratios are approximations. In general, begin with half of the estimated daily morphine requirement as the initial dose, managing inadequate analgesia by supplementation with immediate-release morphine.

Conversion from Methadone to MS CONTIN

Regular evaluation is of particular importance when converting methadone to other opioid agonists. The ratio between methadone and other opioid agonists may vary widely as a function of previous dose exposure. Methadone has a long half-life and can accumulate in the plasma.

Conversion from Other Oral Opioid Analgesics to MS CONTIN

When MS CONTIN therapy is initiated, discontinue all opioid analgesics other than those used on an as needed basis for breakthrough pain when appropriate.

There are no established conversion ratios for conversion from other opioid analgesics to MS CONTIN defined by clinical trials. Initiate dosing using MS CONTIN 15 mg orally every 8 to 12 hours.

2.4 Titration and Maintenance of Therapy

Individually titrate MS CONTIN to a dose that provides adequate analgesia and minimizes adverse reactions. Continually reevaluate patients receiving MS CONTIN to assess the maintenance of pain control, signs and symptoms of opioid withdrawal, and other adverse reactions, as well as to reassess for the development of addiction, abuse, or misuse [see Warnings and Precautions (5.1, 5.14)]. Frequent communication is important among the prescriber, other members of the healthcare team, the patient, and the caregiver/family during periods of changing analgesic requirements, including initial titration. During use of opioid therapy for an extended period of time, periodically reassess the continued need for the use of opioid analgesics.

Patients who experience breakthrough pain may require a dosage adjustment of MS CONTIN or may need rescue medication with an appropriate dose of an immediate-release analgesic.

If the level of pain increases after dose stabilization, attempt to identify the source of increased pain before increasing the MS CONTIN dosage. If after increasing the dosage, unacceptable opioid- related adverse reactions are observed (including an increase in pain after a dosage increase), consider reducing the dosage [see Warnings and Precautions (5)]. Adjust the dosage to obtain an appropriate balance between management of pain and opioid-related adverse reactions.

Because steady-state plasma concentrations are approximated in 1 day, MS CONTIN dosage adjustments may be done every 1 to 2 days.

2.5 Dosage Modifications with Concomitant Use of Central Nervous System Depressants

If the patient is currently taking a central nervous system (CNS) depressant and the decision is made to begin MS CONTIN, start with the lowest possible dose, 15 mg every 12 hours, monitor patients for signs of respiratory depression, sedation, and hypotension, and consider using a lower dosage of the concomitant CNS depressant [see Warnings and Precautions (5.3), Drug Interactions (7)].

2.6 Safe Reduction or Discontinuation of MS CONTIN

Do not rapidly reduce or abruptly discontinue MS CONTIN in patients who may be physically dependent on opioids. Rapid reduction or abrupt discontinuation of opioid analgesics in patients who are physically dependent on opioids has resulted in serious withdrawal symptoms, uncontrolled pain, and suicide. Rapid reduction or abrupt discontinuation has also been associated with attempts to find other sources of opioid analgesics, which may be confused with drug-seeking for abuse. Patients may also attempt to treat their pain or withdrawal symptoms with illicit opioids, such as heroin, and other substances.

When a decision has been made to decrease the dose or discontinue therapy in an opioid dependent patient taking MS CONTIN, there are a variety of factors that should be considered, including the total daily dose of opioid (including MS CONTIN) the patient has been taking, the duration of treatment, the type of pain being treated, and the physical and psychological attributes of the patient. It is important to ensure ongoing care of the patient and to agree on an appropriate tapering schedule and follow-up plan so that patient and provider goals and expectations are clear and realistic. When opioid analgesics are being discontinued due to a suspected substance use disorder, evaluate, and treat the patient, or refer for evaluation and treatment of the substance use disorder. Treatment should include evidence-based approaches, such as medication assisted treatment of opioid use disorder. Complex patients with co-morbid pain and substance use disorders may benefit from referral to a specialist.

There are no standard opioid tapering schedules that are suitable for all patients. Good clinical practice dictates a patient-specific plan to taper the dose of the opioid gradually. For patients on MS CONTIN who are physically opioid-dependent, initiate the taper by a small enough increment (e.g., no greater than 10% to 25% of the total daily dose) to avoid withdrawal symptoms, and proceed with dose-lowering at an interval of every 2 to 4 weeks. Patients who have been taking opioids for briefer periods of time may tolerate a more rapid taper.

It may be necessary to provide the patient with lower dosage strengths to accomplish a successful taper. Reassess the patient frequently to manage pain and withdrawal symptoms, should they emerge. Common withdrawal symptoms include restlessness, lacrimation, rhinorrhea, yawning, perspiration, chills, myalgia, and mydriasis. Other signs and symptoms also may develop, including irritability, anxiety, backache, joint pain, weakness, abdominal cramps, insomnia, nausea, anorexia, vomiting, diarrhea, or increased blood pressure, respiratory rate, or heart rate. If withdrawal symptoms arise, it may be necessary to pause the taper for a period of time or raise the dose of the opioid analgesic to the previous dose, and then proceed with a slower taper. In addition, evaluate patients for any changes in mood, emergence of suicidal thoughts, or use of other substances.

When managing patients taking opioid analgesics, particularly those who have been treated for an extended period of time and/or with high doses for chronic pain, ensure that a multimodal approach to pain management, including mental health support (if needed), is in place prior to initiating an opioid analgesic taper. A multimodal approach to pain management may optimize the treatment of chronic pain, as well as assist with the successful tapering of the opioid analgesic [see Warnings and Precautions (5.14), Drug Abuse and Dependence (9.3)].

3 DOSAGE FORMS AND STRENGTHS

- MS CONTIN® (morphine sulfate extended-release tablets) 15 mg
  Round, blue-colored, film-coated tablets bearing the symbol PF on one side and M 15 on the other
- MS CONTIN® (morphine sulfate extended-release tablets) 30 mg
  Round, lavender-colored, film-coated tablets bearing the symbol PF on one side and M 30 on the other
- MS CONTIN® (morphine sulfate extended-release tablets) 60 mg
  Round, orange-colored, film-coated tablets bearing the symbol PF on one side and M 60 on the other
- MS CONTIN® (morphine sulfate extended-release tablets) 100 mg
  Round, gray-colored, film-coated tablets bearing the symbol PF on one side and 100 on the other
- MS CONTIN® (morphine sulfate extended-release tablets) 200 mg
  Capsule-shaped, green-colored, film-coated tablets bearing the symbol PF on one side and M 200 on the other

4 CONTRAINDICATIONS

MS CONTIN is contraindicated in patients with:

- Significant respiratory depression [see Warnings and Precautions (5.2)]
- Acute or severe bronchial asthma in an unmonitored setting or in the absence of resuscitative equipment [see Warnings and Precautions (5.7)]
- Concurrent use of monoamine oxidase inhibitors (MAOIs) or use of MAOIs within the last 14 days [see Warnings and Precautions (5.8), Drug Interactions (7)].
- Known or suspected gastrointestinal obstruction, including paralytic ileus [see Warnings and Precautions (5.12)]
- Hypersensitivity (e.g., anaphylaxis) to morphine [see Adverse Reactions (6.2)]

5 WARNINGS AND PRECAUTIONS

5.1 Addiction, Abuse, and Misuse

MS CONTIN contains morphine, a Schedule II controlled substance. As an opioid, MS CONTIN exposes its users to the risks of addiction, abuse, and misuse.

Although the risk of addiction in any individual is unknown, it can occur in patients appropriately prescribed MS CONTIN. Addiction can occur at recommended doses and if the drug is misused or abused. The risk of opioid-related overdose or overdose-related death is increased with higher opioid doses, and this risk persists over the course of therapy. In postmarketing studies, addiction, abuse, misuse, and fatal and non-fatal opioid overdose were observed in patients with long-term opioid use [see Adverse Reactions (6.2)].

Assess each patient's risk for opioid addiction, abuse, or misuse prior to prescribing MS CONTIN, and reassess all patients receiving MS CONTIN for development of these behaviors and conditions. Risks are increased in patients with a personal or family history of substance abuse (including drug or alcohol abuse or addiction) or mental illness (e.g., major depression). The potential for these risks should not, however, prevent the proper management of pain in any given patient. Patients at increased risk may be prescribed opioids such as MS CONTIN, but use in such patients necessitates intensive counseling about the risks of proper use of MS CONTIN along with frequent reevaluation for signs of addiction, abuse, and misuse. Consider recommending or prescribing an opioid overdose reversal agent [see Dosage and Administration (2.2), Warnings and Precautions (5.2)].

Abuse or misuse of MS CONTIN by crushing, chewing, snorting, or injecting the dissolved product will result in the uncontrolled delivery of morphine and can result in overdose and death [see Overdosage (10)].

Opioids are sought for nonmedical use and are subject to diversion from legitimate prescribed use. Consider these risks when prescribing or dispensing MS CONTIN. Strategies to reduce these risks include prescribing the drug in the smallest appropriate quantity and advising the patient on careful storage of the drug during the course of treatment and proper disposal of unused drug. Contact local state professional licensing board or state-controlled substances authority for information on how to prevent and detect abuse or diversion of this product.

5.2 Life-Threatening Respiratory Depression

Serious, life-threatening, or fatal respiratory depression has been reported with the use of opioids, even when used as recommended. Respiratory depression, if not immediately recognized and treated, may lead to respiratory arrest and death. Management of respiratory depression may include close observation, supportive measures, and use of opioid overdose reversal agent, depending on the patient's clinical status [see Overdosage (10)]. Carbon dioxide (CO2) retention from opioid-induced respiratory depression can exacerbate the sedating effects of opioids.

While serious, life-threatening, or fatal respiratory depression can occur at any time during the use of MS CONTIN, the risk is greatest during the initiation of therapy or following a dosage increase.

To reduce the risk of respiratory depression, proper dosing and titration of MS CONTIN are essential [see Dosage and Administration (2)]. Overestimating the MS CONTIN dosage when converting patients from another opioid product can result in a fatal overdose with the first dose.

Accidental ingestion of even one dose of MS CONTIN, especially by children, can result in respiratory depression and death due to an overdose of morphine.

Educate patients and caregivers on how to recognize respiratory depression and emphasize the importance of calling 911 or getting emergency medical help right away in the event of a known or suspected overdose.

Opioids can cause sleep-related breathing disorders including central sleep apnea (CSA) and sleep- related hypoxemia. Opioid use increases the risk of CSA in a dose-dependent fashion. In patients who present with CSA, consider decreasing the opioid dosage using best practices for opioid taper [see Dosage and Administration (2.6)].

Patient Access to an Opioid Overdose Reversal Agent for the Emergency Treatment of Opioid Overdose

Inform patients and caregivers about opioid overdose reversal agents (e.g., naloxone, nalmefene). Discuss the importance of having access to an opioid overdose reversal agent, especially if the patient has risk factors for overdose (e.g., concomitant use of CNS depressants, a history of opioid use disorder, or prior opioid overdose) or if there are household members (including children) or other close contacts at risk for accidental ingestion or opioid overdose. The presence of risk factors for overdose should not prevent the management of pain in any patient [see Warnings and Precautions (5.1, 5.3)].

Discuss the options for obtaining an opioid overdose reversal agent (e.g., prescription, over-the-counter, or as part of a community-based program).

There are important differences among the opioid overdose reversal agents, such as route of administration, product strength, approved patient age range, and pharmacokinetics. Be familiar with these differences, as outlined in the approved labeling for those products, prior to recommending or prescribing such an agent.

Educate patients and caregivers on how to recognize respiratory depression, and how to use an opioid overdose reversal agent for the emergency treatment of opioid overdose. Emphasize the importance of calling 911 or getting emergency medical help, even if an opioid overdose reversal agent is administered [see Dosage and Administration (2.2), Warnings and Precautions (5.1, 5.3), Overdosage (10)].

5.3 Risks from Concomitant Use with Benzodiazepines or Other CNS Depressants

Profound sedation, respiratory depression, coma, and death may result from the concomitant use of MS CONTIN with benzodiazepines and/or other CNS depressants, including alcohol (e.g., non-benzodiazepine sedatives/hypnotics, anxiolytics, tranquilizers, muscle relaxants, general anesthetics, antipsychotics, gabapentinoids [gabapentin or pregabalin], and other opioids). Because of these risks, reserve concomitant prescribing of these drugs for use in patients for whom alternative treatment options are inadequate.

Observational studies have demonstrated that concomitant use of opioid analgesics and benzodiazepines increases the risk of drug-related mortality compared to use of opioid analgesics alone. Because of similar pharmacological properties, it is reasonable to expect similar risk with the concomitant use of other CNS depressant drugs with opioid analgesics [see Drug Interactions (7)].

If the decision is made to prescribe a benzodiazepine or other CNS depressant concomitantly with an opioid analgesic, prescribe the lowest effective dosages and minimum durations of concomitant use. In patients already receiving an opioid analgesic, prescribe a lower initial dose of the benzodiazepine or other CNS depressant than indicated in the absence of an opioid, and titrate based on clinical response. If an opioid analgesic is initiated in a patient already taking a benzodiazepine or other CNS depressant, prescribe a lower initial dose of the opioid analgesic, and titrate based on clinical response. Inform patients and caregivers of this potential interaction and educate them on the signs and symptoms of respiratory depression (including sedation).

If concomitant use is warranted, consider recommending or prescribing an opioid overdose reversal agent [see Dosage and Administration (2.2), Warning and Precautions (5.2), see Overdosage (10)].

Advise both patients and caregivers about the risks of respiratory depression and sedation when MS CONTIN is used with benzodiazepines or other CNS depressants (including alcohol and illicit drugs). Advise patients not to drive or operate heavy machinery until the effects of concomitant use of the benzodiazepine or other CNS depressant have been determined. Screen patients for risk of substance use disorders, including opioid abuse and misuse, and warn them of the risk for overdose and death associated with the use of additional CNS depressants including alcohol and illicit drugs [see Drug Interactions (7)].

5.4 Neonatal Opioid Withdrawal Syndrome

Use of MS CONTIN for an extended period of time during pregnancy can result in withdrawal in the neonate. Neonatal opioid withdrawal syndrome, unlike opioid withdrawal syndrome in adults, may be life-threatening if not recognized and treated, and requires management according to protocols developed by neonatology experts. Observe newborns for signs of neonatal opioid withdrawal syndrome and manage accordingly. Advise pregnant women using opioids for an extended period of time of the risk of neonatal opioid withdrawal syndrome and ensure that appropriate treatment will be available [see Use In Specific Populations (8.1)].

5.5 Opioid Analgesic Risk Evaluation and Mitigation Strategy (REMS)

To ensure that the benefits of opioid analgesics outweigh the risks of addiction, abuse, and misuse, the Food and Drug Administration (FDA) has required a Risk Evaluation and Mitigation Strategy (REMS) for these products. Under the requirements of the REMS, drug companies with approved opioid analgesic products must make REMS-compliant education programs available to healthcare providers. Healthcare providers are strongly encouraged to do all of the following:

- Complete a REMS-compliant education program offered by an accredited provider of continuing education (CE) or another education program that includes all the elements of the FDA Education Blueprint for Health Care Providers Involved in the Management or Support of Patients with Pain.
- Discuss the safe use, serious risks, and proper storage and disposal of opioid analgesics with patients and/or their caregivers every time these medicines are prescribed. The Patient Counseling Guide (PCG) can be obtained at this link: www.fda.gov/OpioidAnalgesicREMSPCG.
- Emphasize to patients and their caregivers the importance of reading the Medication Guide that they will receive from their pharmacist every time an opioid analgesic is dispensed to them.
- Consider using other tools to improve patient, household, and community safety, such as patient- prescriber agreements that reinforce patient-prescriber responsibilities.
- To obtain further information on the opioid analgesic REMS and for a list of accredited REMS CME/CE, call 1-800-503-0784, or log on to www.opioidanalgesicrems.com. The FDA Blueprint can be found at www.fda.gov/OpioidAnalgesicREMSBlueprint.

5.6 Opioid-Induced Hyperalgesia and Allodynia

Opioid-Induced Hyperalgesia (OIH) occurs when an opioid analgesic paradoxically causes an increase in pain, or an increase in sensitivity to pain. This condition differs from tolerance, which is the need for increasing doses of opioids to maintain a defined effect [see Drug Abuse and Dependence (9.3)].

Symptoms of OIH include (but may not be limited to) increased levels of pain upon opioid dosage increase, decreased levels of pain upon opioid dosage decrease, or pain from ordinarily non-painful stimuli (allodynia). These symptoms may suggest OIH only if there is no evidence of underlying disease progression, opioid tolerance, opioid withdrawal, or addictive behavior.

Cases of OIH have been reported, both with short-term and longer-term use of opioid analgesics. Though the mechanism of OIH is not fully understood, multiple biochemical pathways have been implicated. Medical literature suggests a strong biologic plausibility between opioid analgesics and OIH and allodynia. If a patient is suspected to be experiencing OIH, carefully consider appropriately decreasing the dose of the current opioid analgesic or opioid rotation (safely switching the patient to a different opioid moiety) [see Dosage and Administration (2.6), Warnings and Precautions (5.14)].

5.7 Risk of Life-Threatening Respiratory Depression in Patients with Chronic Pulmonary Disease or in Elderly, Cachectic, or Debilitated Patients

The use of MS CONTIN in patients with acute or severe bronchial asthma in an unmonitored setting or in the absence of resuscitative equipment is contraindicated.

Patients with Chronic Pulmonary Disease: MS CONTIN-treated patients with significant chronic obstructive pulmonary disease or cor pulmonale, and those with a substantially decreased respiratory reserve, hypoxia, hypercapnia, or pre-existing respiratory depression are at increased risk of decreased respiratory drive including apnea, even at recommended dosages of MS CONTIN [see Warnings and Precautions (5.2)].

Elderly, Cachectic, or Debilitated Patients: Life-threatening respiratory depression is more likely to occur in elderly, cachectic, or debilitated patients as they may have altered pharmacokinetics or altered clearance compared to younger, healthier patients [see Warnings and Precautions (5.2)].

Regularly evaluate patients, particularly when initiating and titrating MS CONTIN and when MS CONTIN is given concomitantly with other drugs that depress respiration [see Warnings and Precautions (5.3), Drug Interactions (7)]. Alternatively, consider the use of non-opioid analgesics in these patients.

5.8 Interaction with Monoamine Oxidase Inhibitors

Monoamine oxidase inhibitors (MAOIs) may potentiate the effects of morphine, including respiratory depression, coma, and confusion. MS CONTIN should not be used in patients taking MAOIs or within 14 days of stopping such treatment.

5.9 Adrenal Insufficiency

Cases of adrenal insufficiency have been reported with opioid use, more often following greater than one month of use. Presentation of adrenal insufficiency may include non-specific symptoms and signs including nausea, vomiting, anorexia, fatigue, weakness, dizziness, and low blood pressure. If adrenal insufficiency is suspected, confirm the diagnosis with diagnostic testing as soon as possible. If adrenal insufficiency is diagnosed, treat with physiologic replacement doses of corticosteroids. Wean the patient off of the opioid to allow adrenal function to recover and continue corticosteroid treatment until adrenal function recovers. Other opioids may be tried as some cases reported use of a different opioid without recurrence of adrenal insufficiency. The information available does not identify any particular opioids as being more likely to be associated with adrenal insufficiency.

5.10 Severe Hypotension

MS CONTIN may cause severe hypotension including orthostatic hypotension and syncope in ambulatory patients. There is increased risk in patients whose ability to maintain blood pressure has already been compromised by a reduced blood volume or concurrent administration of certain CNS depressant drugs (e.g., phenothiazines or general anesthetics) [see Drug Interactions (7)].

Regularly evaluate these patients for signs of hypotension after initiating or titrating the dosage of MS CONTIN. In patients with circulatory shock, MS CONTIN may cause vasodilation that can further reduce cardiac output and blood pressure. Avoid the use of MS CONTIN in patients with circulatory shock.

5.11 Risks of Use in Patients with Increased Intracranial Pressure, Brain Tumors, Head Injury, or Impaired Consciousness

In patients who may be susceptible to the intracranial effects of CO2 retention (e.g., those with evidence of increased intracranial pressure or brain tumors), MS CONTIN may reduce respiratory drive, and the resultant CO2 retention can further increase intracranial pressure. Regularly evaluate such patients for signs of sedation and respiratory depression, particularly when initiating therapy with MS CONTIN.

Opioids may also obscure the clinical course in a patient with a head injury. Avoid the use of MS CONTIN in patients with impaired consciousness or coma.

5.12 Risks of Gastrointestinal Complications

MS CONTIN is contraindicated in patients with known or suspected gastrointestinal obstruction, including paralytic ileus.

The morphine in MS CONTIN may cause spasm of the sphincter of Oddi. Opioids may cause increases in serum amylase. Regularly evaluate patients with biliary tract disease, including acute pancreatitis, for worsening symptoms.

Cases of opioid-induced esophageal dysfunction (OIED) have been reported in patients taking opioids. The risk of OIED may increase as the dose and/or duration of opioids increases. Regularly evaluate patients for signs and symptoms of OIED (e.g., dysphagia, regurgitation, non-cardiac chest pain) and, if necessary, adjust opioid therapy as clinically appropriate [see Clinical Pharmacology(12.2)].

5.13 Increased Risk of Seizures in Patients with Seizure Disorders

The morphine in MS CONTIN may increase the frequency of seizures in patients with seizure disorders, and may increase the risk of seizures occurring in other clinical settings associated with seizures. Regularly evaluate patients with a history of seizure disorders for worsened seizure control during MS CONTIN therapy.

5.14 Withdrawal

Do not rapidly reduce or abruptly discontinue MS CONTIN in a patient physically dependent on opioids. When discontinuing MS CONTIN in a physically dependent patient, gradually taper the dosage. Rapid tapering of morphine in a patient physically dependent on opioids may lead to a withdrawal syndrome and return of pain [see Dosage and Administration (2.6), Drug Abuse and Dependence (9.3)].

Additionally, avoid the use of mixed agonist/antagonist (e.g., pentazocine, nalbuphine, and butorphanol) or partial agonist (e.g., buprenorphine) analgesics in patients who have received or are receiving a course of therapy with a full opioid agonist analgesic, including MS CONTIN. In these patients, mixed agonists/antagonist and partial agonist analgesics may reduce the analgesic effect and/or may precipitate withdrawal symptoms [see Drug Interactions (7)].

5.15 Risks of Driving and Operating Machinery

MS CONTIN may impair the mental or physical abilities needed to perform potentially hazardous activities such as driving a car or operating machinery. Warn patients not to drive or operate dangerous machinery unless they are tolerant to the effects of MS CONTIN and know how they will react to the medication.

6 ADVERSE REACTIONS

The following serious adverse reactions are described, or described in greater detail, in other sections:

- Addiction, Abuse, and Misuse [see Warnings and Precautions (5.1)]
- Life-Threatening Respiratory Depression [see Warnings and Precautions (5.2)]
- Interactions with Benzodiazepine or Other CNS Depressants [see Warnings and Precautions (5.3)]
- Neonatal Opioid Withdrawal Syndrome [see Warnings and Precautions (5.4)]
- Opioid-Induced Hyperalgesia and Allodynia [see Warnings and Precautions (5.6)]
- Adrenal Insufficiency [see Warnings and Precautions (5.9)]
- Severe Hypotension [see Warnings and Precautions (5.10)]
- Gastrointestinal Adverse Reactions [see Warnings and Precautions (5.12)]
- Seizures [see Warnings and Precautions (5.13)]
- Withdrawal [see Warnings and Precautions (5.14)]

6.1 Clinical Trial Experience

Because clinical trials are conducted under widely varying conditions, adverse reaction rates observed in the clinical trials of a drug cannot be directly compared to rates in the clinical trials of another drug and may not reflect the rates observed in practice.

MS CONTIN may increase the risk of serious adverse reactions such as those observed with other opioid analgesics, including respiratory depression, apnea, respiratory arrest, circulatory depression, hypotension, or shock [see Overdosage (10)].

Most Frequently Observed Reactions

In clinical trials, the most common adverse reactions with MS CONTIN were constipation, dizziness, sedation, nausea, vomiting, sweating, dysphoria, and euphoric mood.

Some of these effects seem to be more prominent in ambulatory patients and in those not experiencing severe pain.

Less Frequently Observed Reactions

Cardiovascular disorders: tachycardia, bradycardia, palpitations

Eye disorders: visual impairment, vision blurred, diplopia, miosis

Gastrointestinal disorders: dry mouth, diarrhea, abdominal pain, constipation, dyspepsia

General disorders and administration site conditions: chills, feeling abnormal, edema, edema peripheral, weakness

Hepatobiliary disorders: biliary colic

Metabolism and nutrition disorders: anorexia

Musculoskeletal and connective tissue disorders: muscle rigidity, muscle twitching

Nervous system disorders: presyncope, syncope, headache, tremor, uncoordinated muscle movements, convulsion, intracranial pressure increased, taste alteration, paresthesia, nystagmus

Psychiatric disorders: agitation, mood altered, anxiety, depression, abnormal dreams, hallucination, disorientation, insomnia

Renal and urinary disorders: urinary retention, urinary hesitation, antidiuretic effects Reproductive system and breast disorders: reduced libido and/or potency Respiratory, thoracic, and mediastinal disorders: laryngospasm

Skin and subcutaneous tissue disorders: pruritus, urticaria, rash

Vascular disorders: flushing, hypotension, hypertension

6.2 Post-Marketing Experience

The following adverse reactions have been identified during post-approval use of MS CONTIN. Because these reactions are reported voluntarily from a population of uncertain size, it is not always possible to reliably estimate their frequency or establish a causal relationship to drug exposure.

Amenorrhea, asthenia, bronchospasm, confusional state, drug hypersensitivity, fatigue, hyperalgesia, hypertonia, ileus, increased hepatic enzymes, intestinal obstruction, lethargy, malaise, pulmonary edema, thinking disturbances, somnolence, and vertigo.

Serotonin syndrome: Cases of serotonin syndrome, a potentially life-threatening condition, have been reported during concomitant use of opioids with serotonergic drugs.

Adrenal insufficiency: Cases of adrenal insufficiency have been reported with opioid use, more often following greater than one month of use.

Anaphylaxis: Anaphylaxis has been reported with ingredients contained in MS CONTIN.

Androgen deficiency: Cases of androgen deficiency have occurred with use of opioids for an extended period of time [see Clinical Pharmacology (12.2)].

Hyperalgesia and Allodynia: Cases of hyperalgesia and allodynia have been reported with opioid therapy of any duration [see Warnings and Precautions (5.6)].

Hypoglycemia: Cases of hypoglycemia have been reported in patients taking opioids. Most reports were in patients with at least one predisposing risk factor (e.g., diabetes).

Opioid-induced esophageal dysfunction (OIED): Cases of OIED have been reported in patients taking opioids and may occur more frequently in patients taking higher doses of opioids, and/or in patients taking opioids longer term [see Warnings and Precautions (5.12)].

Adverse Reactions from Observational Studies

A prospective, observational cohort study estimated the risks of addiction, abuse, and misuse in patients initiating long-term use of Schedule II opioid analgesics between 2017 and 2021. Study participants included in one or more analyses had been enrolled in selected insurance plans or health systems for at least one year, were free of at least one outcome at baseline, completed a minimum number of follow-up assessments, and either: 1) filled multiple extended-release/long-acting opioid analgesic prescriptions during a 90-day period (n=978); or 2) filled any Schedule II opioid analgesic prescriptions covering at least 70 of 90 days (n=1,244). Those included also had no dispensing of the qualifying opioids in the previous 6 months.

Over 12 months:

- approximately 1% to 6% of participants across the two cohorts newly met criteria for addiction, as assessed with two validated interview-based measures of moderate-to-severe opioid use disorder based on Diagnostic and Statistical Manual of Mental Disorders, Fifth Edition (DSM-5) criteria, and
- approximately 9% and 22% of participants across the two cohorts newly met criteria for prescription opioid abuse and misuse [defined in Drug Abuse and Dependence (9.2)], respectively, as measured with a validated self-reported instrument.

A retrospective, observational cohort study estimated the risk of opioid-involved overdose or opioid overdose-related death in patients with new long-term use of Schedule II opioid analgesics from 2006 through 2016 (n=220,249). Included patients had been enrolled in either one of two commercial insurance programs, one managed care program, or one Medicaid program for at least 9 months. New long-term use was defined as having Schedule II opioid analgesic prescriptions covering at least 70 days' supply over the 3 months prior to study entry and none during the preceding 6 months. Patients were excluded if they had an opioid-involved overdose in the 9 months prior to study entry. Overdose was measured using a validated medical code-based algorithm with linkage to the National Death Index database. The 5-year cumulative incidence estimates for opioid-involved overdose or opioid overdose-related death ranged from approximately 1.5% to 4% across study sites, counting only the first event during follow-up. Approximately 17% of first opioid overdoses observed over the entire study period (5 to 11 years, depending on the study site) were fatal. Higher baseline opioid dose was the strongest and most consistent predictor of opioid-involved overdose or opioid overdose-related death. Study exclusion criteria may have selected patients at lower risk of overdose, and substantial loss to follow-up (approximately 80%) also may have biased estimates.

The risk estimates from the studies described above may not be generalizable to all patients receiving opioid analgesics, such as those with exposures shorter or longer than the duration evaluated in the studies.

7 DRUG INTERACTIONS

Table 1 includes clinically significant drug interactions with MS CONTIN.

Table 1: Clinically Significant Drug Interactions with MS CONTIN
Benzodiazepines and Other Central Nervous System (CNS) Depressants
Clinical Impact: | Due to additive pharmacologic effect, the concomitant use of benzodiazepines or other CNS depressants, including alcohol, can increase the risk of hypotension, respiratory depression, profound sedation, coma, and death [see Warnings and Precautions (5.3)].
Intervention: | Reserve concomitant prescribing of these drugs for use in patients for whom alternative treatment options are inadequate. Limit dosages and durations to the minimum required. Inform patients and caregivers of this potential interaction and educate them on the signs and symptoms of respiratory depression (including sedation). If concomitant use is warranted, consider recommending or prescribing an opioid overdose reversal agent [see Dosage and Administration (2.2, 2.5), Warnings and Precautions (5.1, 5.2, 5.3)].
Examples: | Benzodiazepines and other sedative hypnotics, anxiolytics, tranquilizers, muscle relaxants, general anesthetics, antipsychotics, gabapentinoids (gabapentin or pregabalin), other opioids, alcohol.
Serotonergic Drugs
Clinical Impact: | The concomitant use of opioids with other drugs that affect the serotonergic neurotransmitter system has resulted in serotonin syndrome.
Intervention: | If concomitant use is warranted, frequently evaluate the patient, particularly during treatment initiation and dose adjustment. Discontinue MS CONTIN if serotonin syndrome is suspected.
Examples: | Selective serotonin reuptake inhibitors (SSRIs), serotonin and norepinephrine reuptake inhibitors (SNRIs), tricyclic antidepressants (TCAs), triptans, 5-HT3 receptor antagonists, drugs that effect the serotonin neurotransmitter system (e.g., mirtazapine, trazodone, tramadol), certain muscle relaxants (i.e., cyclobenzaprine, metaxalone), monoamine oxidase (MAO) inhibitors (those intended to treat psychiatric disorders and also others, such as linezolid and intravenous methylene blue).
Monoamine Oxidase Inhibitors (MAOIs)
Clinical Impact: | MAOI interactions with opioids may manifest as serotonin syndrome or opioid toxicity (e.g., respiratory depression, coma) [see Warnings and Precautions (5.8)].
Intervention: | Do not use MS CONTIN in patients taking MAOIs or within 14 days of stopping such treatment.
Examples: | phenelzine, tranylcypromine, linezolid
Mixed Agonist/Antagonist and Partial Agonist Opioid Analgesics
Clinical Impact: | May reduce the analgesic effect of MS CONTIN and/or precipitate withdrawal symptoms.
Intervention: | Avoid concomitant use.
Examples: | butorphanol, nalbuphine, pentazocine, buprenorphine
Muscle Relaxants
Clinical Impact: | Morphine may enhance the neuromuscular blocking action of skeletal muscle relaxants and produce an increased degree of respiratory depression.
Intervention: | Because respiratory depression may be greater than otherwise expected, decrease the dosage of MS CONTIN and/or the muscle relaxant as necessary. Due to the risk of respiratory depression with concomitant use of skeletal muscle relaxants and opioids, consider recommending or prescribing an opioid overdose reversal agent [see Dosage and Administration (2.2), Warnings and Precautions (5.2, 5.3)].
Examples | cyclobenzaprine, metaxalone
Cimetidine
Clinical Impact: | The concomitant use of cimetidine can potentiate morphine effects and increase risk of hypotension, respiratory depression, profound sedation, coma, and death.
Intervention: | Evaluate patients for signs of respiratory depression that may be greater than otherwise expected and decrease the dosage of MS CONTIN and/or cimetidine as necessary.
Diuretics
Clinical Impact: | Opioids can reduce the efficacy of diuretics by inducing the release of antidiuretic hormone.
Intervention: | Evaluate patients for signs of diminished diuresis and/or effects on blood pressure and increase the dosage of the diuretic as needed.
Anticholinergic Drugs
Clinical Impact: | The concomitant use of anticholinergic drugs may increase risk of urinary retention and/or severe constipation, which may lead to paralytic ileus.
Intervention: | Evaluate patients for signs of urinary retention or reduced gastric motility when MS CONTIN is used concomitantly with anticholinergic drugs.
P-Glycoprotein (P-gp) Inhibitors
Clinical Impact: | The concomitant use of PGP-inhibitors can increase the exposure to morphine by about two-fold and can increase risk of hypotension, respiratory depression, profound sedation, coma, and death.
Intervention: | Evaluate patients for signs of respiratory depression that may be greater than otherwise expected and decrease the dosage of MS CONTIN and/or the PGP- inhibitor as necessary.
Example: | quinidine

8 USE IN SPECIFIC POPULATIONS

8.1 Pregnancy

Risk Summary

Use of opioid analgesics for an extended period of time during pregnancy may cause neonatal withdrawal syndrome [see Warnings And Precautions(5.4)]. There are no available data with MS CONTIN in pregnant women to inform a drug-associated risk for major birth defects and miscarriage. Published studies with morphine use during pregnancy have not reported a clear association with morphine and major birth defects [see Human Data]. In published animal reproduction studies, morphine administered subcutaneously during the early gestational period produced neural tube defects (i.e., exencephaly and cranioschisis) at 5 and 16 times the human daily dose of 60 mg based on body surface area (HDD) in hamsters and mice, respectively, lower fetal body weight and increased incidence of abortion at 0.4 times the HDD in the rabbit, growth retardation at 6 times the HDD in the rat, and axial skeletal fusion and cryptorchidism at 16 times the HDD in the mouse. Administration of morphine sulfate to pregnant rats during organogenesis and through lactation resulted in cyanosis, hypothermia, decreased brain weights, pup mortality, decreased pup body weights, and adverse effects on reproductive tissues at 3 to 4 times the HDD; and long-term neurochemical changes in the brain of offspring which correlate with altered behavioral responses that persist through adulthood at exposures comparable to and less than the HDD [see Animal Data]. Based on animal data, advise pregnant women of the potential risk to a fetus.

The background risk of major birth defects and miscarriage for the indicated population is unknown. All pregnancies have a background risk of birth defect, loss, or other adverse outcomes. In the U.S. general population, the estimated background risk of major birth defects and miscarriage in clinically recognized pregnancies is 2 to 4% and 15 to 20%, respectively.

Clinical Considerations

Fetal/Neonatal Adverse Reactions

Use of opioid analgesics for an extended period of time during pregnancy for medical or nonmedical purposes can result in physical dependence in the neonate and neonatal opioid withdrawal syndrome shortly after birth. Neonatal opioid withdrawal syndrome presents as irritability, hyperactivity and abnormal sleep pattern, high pitched cry, tremor, vomiting, diarrhea, and failure to gain weight. The onset, duration, and severity of neonatal opioid withdrawal syndrome vary based on the specific opioid used, duration of use, timing and amount of last maternal use, and rate of elimination of the drug by the newborn. Observe newborns for symptoms of neonatal opioid withdrawal syndrome and manage accordingly [see Warnings and Precautions (5.4)].

Labor or Delivery

Opioids cross the placenta and may produce respiratory depression and psycho-physiologic effects in neonates. An opioid overdose reversal agent, such as naloxone or nalmefene, must be available for reversal of opioid-induced respiratory depression in the neonate. MS CONTIN is not recommended for use in pregnant women during or immediately prior to labor, when use of shorter-acting analgesics or other analgesic techniques are more appropriate. Opioid analgesics, including MS CONTIN, can prolong labor through actions which temporarily reduce the strength, duration, and frequency of uterine contractions. However, this effect is not consistent and may be offset by an increased rate of cervical dilation, which tends to shorten labor. Monitor neonates exposed to opioid analgesics during labor for signs of excess sedation and respiratory depression.

Data

Human Data

The results from a population-based prospective cohort, including 70 women exposed to morphine during the first trimester of pregnancy and 448 women exposed to morphine at any time during pregnancy, indicate no increased risk for congenital malformations. However, these studies cannot definitely establish the absence of any risk because of methodological limitations, including small sample size and non-randomized study design.

Animal Data

Formal reproductive and developmental toxicology studies for morphine have not been conducted. Exposure margins for the following published study reports are based on human daily dose of 60 mg morphine using a body surface area comparison (HDD).

Neural tube defects (exencephaly and cranioschisis) were noted following subcutaneous administration of morphine sulfate (35 to 322 mg/kg) on Gestation Day 8 to pregnant hamsters (4.7 to 43.5 times the HDD). A no adverse effect level was not defined in this study and the findings cannot be clearly attributed to maternal toxicity. Neural tube defects (exencephaly), axial skeletal fusions, and cryptorchidism were reported following a single subcutaneous (SC) injection of morphine sulfate to pregnant mice (100 to 500 mg/kg) on Gestation Day 8 or 9 at 200 mg/kg or greater (16 times the HDD) and fetal resorption at 400 mg/kg or higher (32 times the HDD). No adverse effects were noted following 100 mg/kg morphine in this model (8 times the HDD). In one study, following continuous subcutaneous infusion of doses greater than or equal to 2.72 mg/kg to mice (0.2 times the HDD), exencephaly, hydronephrosis, intestinal hemorrhage, split supraoccipital, malformed sternebrae, and malformed xiphoid were noted. The effects were reduced with increasing daily dose, possibly due to rapid induction of tolerance under these infusion conditions. The clinical significance of this report is not clear.

Decreased fetal weights were observed in pregnant rats treated with 20 mg/kg/day morphine sulfate (3.2 times the HDD) from Gestation Day 7 to 9. There was no evidence of malformations despite maternal toxicity (10% mortality). In a second rat study, decreased fetal weight and increased incidences of growth retardation were noted at 35 mg/kg/day (5.7 times the HDD) and there was a reduced number of fetuses at 70 mg/kg/day (11.4 times the HDD) when pregnant rats were treated with 10, 35, or 70 mg/kg/day morphine sulfate via continuous infusion from Gestation Day 5 to 20. There was no evidence of fetal malformations or maternal toxicity.

An increased incidence of abortion was noted in a study in which pregnant rabbits were treated with 2.5 (0.8 times the HDD) to 10 mg/kg morphine sulfate via subcutaneous injection from Gestation Day 6 to 10. In a second study, decreased fetal body weights were reported following treatment of pregnant rabbits with increasing doses of morphine (10 to 50 mg/kg/day) during the pre-mating period and 50 mg/kg/day (16 times the HDD) throughout the gestation period. No overt malformations were reported in either publication; although only limited endpoints were evaluated.

In published studies in rats, exposure to morphine during gestation and/or lactation periods is associated with: decreased pup viability at 12.5 mg/kg/day or greater (2 times the HDD); decreased pup body weights at 15 mg/kg/day or greater (2.4 times the HDD); decreased litter size, decreased absolute brain and cerebellar weights, cyanosis, and hypothermia at 20 mg/kg/day (3.2 times the HDD); alteration of behavioral responses (play, social-interaction) at 1 mg/kg/day or greater (0.2 times the HDD); alteration of maternal behaviors (e.g., decreased nursing and pup retrievals) in mice at 1 mg/kg or higher (0.08 times the HDD) and rats at 1.5 mg/kg/day or higher (0.2 times the HDD); and a host of behavioral abnormalities in the offspring of rats, including altered responsiveness to opioids at 4 mg/kg/day (0.7 times the HDD) or greater.

Fetal and/or postnatal exposure to morphine in mice and rats has been shown to result in morphological changes in fetal and neonatal brain and neuronal cell loss, alteration of a number of neurotransmitter and neuromodulator systems, including opioid and non-opioid systems, and impairment in various learning and memory tests that appear to persist into adulthood. These studies were conducted with morphine treatment usually in the range of 4 to 20 mg/kg/day (0.7 to 3.2 times the HDD).

Additionally, delayed sexual maturation and decreased sexual behaviors in female offspring at 20 mg/kg/day (3.2 times the HDD), and decreased plasma and testicular levels of luteinizing hormone and testosterone, decreased testes weights, seminiferous tubule shrinkage, germinal cell aplasia, and decreased spermatogenesis in male offspring were also observed at 20 mg/kg/day (3.2 times the HDD). Decreased litter size and viability were observed in the offspring of male rats that were intraperitoneally administered morphine sulfate for 1 day prior to mating at 25 mg/kg/day (4.1 times the HDD) and mated to untreated females. Decreased viability and body weight and/or movement deficits in both first- and second-generation offspring were reported when male mice were treated for 5 days with escalating doses of 120 to 240 mg/kg/day morphine sulfate (9.7 to 19.5 times the HDD) or when female mice treated with escalating doses of 60 to 240 mg/kg/day (4.9 to 19.5 times the HDD) followed by a 5-day treatment-free recovery period prior to mating. Similar multigenerational findings were also seen in female rats pre-gestationally treated with escalating doses of 10 to 22 mg/kg/day morphine (1.6 to 3.6 times the HDD).

8.2 Lactation

Risk Summary

Morphine is present in breast milk. Published lactation studies report variable concentrations of morphine in breast milk with administration of immediate-release morphine to nursing mothers in the early postpartum period with a milk-to-plasma morphine AUC ratio of 2.5:1 measured in one lactation study. However, there is insufficient information to determine the effects of morphine on the breastfed infant and the effects of morphine on milk production. Lactation studies have not been conducted with extended-release morphine, including MS Contin. Because of the potential for serious adverse reactions, including excess sedation and respiratory depression in a breastfed infant, advise patients that breastfeeding is not recommended during treatment with MS CONTIN.

Clinical Considerations

Monitor infants exposed to MS CONTIN through breast milk for excess sedation and respiratory depression. Withdrawal symptoms can occur in breastfed infants when maternal administration of an opioid analgesic is stopped, or when breastfeeding is stopped.

8.3 Females and Males of Reproductive Potential

Infertility

Use of opioids for an extended period of time may cause reduced fertility in females and males of reproductive potential. It is not known whether these effects on fertility are reversible [see Adverse Reactions (6.2), Clinical Pharmacology (12.2), Nonclinical Toxicology (13.1)].

In published animal studies, morphine administration adversely effected fertility and reproductive endpoints in male rats and prolonged estrus cycle in female rats [see Nonclinical Toxicology (13)].

8.4 Pediatric Use

The safety and effectiveness in pediatric patients below the age of 18 have not been established.

8.5 Geriatric Use

The pharmacokinetics of MS CONTIN have not been studied in elderly patients. Clinical studies of MS CONTIN did not include sufficient numbers of subjects aged 65 and over to determine whether they respond differently from younger subjects.

Elderly patients (aged 65 years or older) may have increased sensitivity to morphine. In general, use caution when selecting a dosage for an elderly patient, usually starting at the low end of the dosing range, reflecting the greater frequency of decreased hepatic, renal, or cardiac function and of concomitant disease or other drug therapy.

Respiratory depression is the chief risk for elderly patients treated with opioids, and has occurred after large initial doses were administered to patients who were not opioid-tolerant or when opioids were co-administered with other agents that depress respiration. Titrate the dosage of MS CONTIN slowly in geriatric patients and frequently reevaluate the patient for signs of central nervous system and respiratory depression [see Warnings And Precautions (5.7)].

Morphine is known to be substantially excreted by the kidney, and the risk of adverse reactions to this drug may be greater in patients with impaired renal function. Because elderly patients are more likely to have decreased renal function, care should be taken in dose selection, and it may be useful to regularly evaluate renal function.

8.6 Hepatic Impairment

Morphine pharmacokinetics have been reported to be significantly altered in patients with cirrhosis. Start these patients with a lower than usual dosage of MS CONTIN and titrate slowly while regularly evaluating for signs of respiratory depression, sedation, and hypotension [see Clinical Pharmacology (12.3)].

8.7 Renal Impairment

Morphine pharmacokinetics are altered in patients with renal failure. Start these patients with a lower than usual dosage of MS CONTIN and titrate slowly while regularly evaluating for signs of respiratory depression, sedation, and hypotension [see Clinical Pharmacology (12.3)].

9 DRUG ABUSE AND DEPENDENCE

9.1 Controlled Substance

MS CONTIN contains morphine, a Schedule II controlled substance.

9.2 Abuse

MS CONTIN contains morphine, a substance with a high potential for misuse and abuse, which can lead to the development of substance use disorder, including addiction [see Warnings and Precautions (5.1)].

Misuse is the intentional use, for therapeutic purposes, of a drug by an individual in a way other than prescribed by a health care provider or for whom it was not prescribed.

Abuse is the intentional, non-therapeutic use of a drug, even once, for its desirable psychological or physiological effects.

Drug addiction is a cluster of behavioral, cognitive, and physiological phenomena that may include a strong desire to take the drug, difficulties in controlling drug use (e.g., continuing drug use despite harmful consequences, giving a higher priority to drug use than to other activities and obligations), and possible tolerance or physical dependence.

Misuse and abuse of MS CONTIN increases risk of overdose, which may lead to central nervous system and respiratory depression, hypotension, seizures, and death. The risk is increased with concurrent abuse of MS CONTIN with alcohol and/or other CNS depressants. Abuse of and addiction to opioids in some individuals may not be accompanied by concurrent tolerance and symptoms of physical dependence. In addition, abuse of opioids can occur in the absence of addiction.

All patients treated with opioids require careful and frequent reevaluation for signs of misuse, abuse, and addiction, because use of opioid analgesic products carries the risk of addiction even under appropriate medical use. Patients at high risk of MS CONTIN abuse include those with a history of prolonged use of any opioid, including products containing morphine, those with a history of drug or alcohol abuse, or those who use MS CONTIN in combination with other abused drugs.

"Drug-seeking" behavior is very common in persons with substance use disorders. Drug-seeking tactics include emergency calls or visits near the end of office hours, refusal to undergo appropriate examination, testing, or referral, repeated "loss" of prescriptions, tampering with prescriptions and reluctance to provide prior medical records or contact information for other healthcare provider(s). "Doctor shopping" (visiting multiple prescribers to obtain additional prescriptions) is common among people who abuse drugs and people with substance use disorder. Preoccupation with achieving adequate pain relief can be appropriate behavior in a patient with poor pain control.

MS CONTIN, like other opioids, can be diverted for nonmedical use into illicit channels of distribution. Careful record-keeping of prescribing information, including quantity, frequency, and renewal requests, as required by state and federal law, is strongly advised.

Proper assessment of the patient, proper prescribing practices, periodic reevaluation of therapy, and proper dispensing and storage are appropriate measures that help to limit abuse of opioid drugs.

Risks Specific to Abuse of MS CONTIN

Abuse of MS CONTIN poses a risk of overdose and death. This risk is increased with concurrent use of MS CONTIN with alcohol and/or other CNS depressants [see Warnings and Precautions (5.1, 5.3), Drug Interactions (7)]. Taking cut, broken, chewed, crushed, or dissolved MS CONTIN enhances drug release and increases the risk of overdose and death.

MS CONTIN is approved for oral use only.

Due to the presence of talc as one of the excipients in MS CONTIN, parenteral abuse can be expected to result in local tissue necrosis, infection, pulmonary granulomas, embolism and death, and increased risk of endocarditis and valvular heart injury.

Parenteral drug abuse is commonly associated with transmission of infectious diseases such as hepatitis and HIV.

9.3 Dependence

Both tolerance and physical dependence can develop during use of opioid therapy.

Tolerance is a physiological state characterized by a reduced response to a drug after repeated administration (i.e., a higher dose of a drug is required to produce the same effect that was once obtained at a lower dose).

Physical dependence is a state that develops as a result of a physiological adaptation in response to repeated drug use, manifested by withdrawal signs and symptoms after abrupt discontinuation or a significant dose reduction of a drug.

Withdrawal may be precipitated through the administration of drugs with opioid antagonist activity, (e.g., naloxone, nalmefene), mixed agonist/antagonist analgesics (e.g., pentazocine, butorphanol, nalbuphine), or partial agonists (e.g., buprenorphine). Physical dependence may not occur to a clinically significant degree until after several days to weeks of continued use.

Do not rapidly reduce or abruptly discontinue MS CONTIN in a patient physically dependent on opioids. Rapid tapering of MS CONTIN in a patient physically dependent on opioids may lead to serious withdrawal symptoms, uncontrolled pain, and suicide. Rapid discontinuation has also been associated with attempts to find other sources of opioid analgesics, which may be confused with drug-seeking for abuse.

When discontinuing MS CONTIN, gradually taper the dosage using a patient-specific plan that considers the following: the dose of MS CONTIN the patient has been taking, the duration of treatment, and the physical and psychological attributes of the patient. To improve the likelihood of a successful taper and minimize withdrawal symptoms, it is important that the opioid tapering schedule is agreed upon by the patient. In patients taking opioids for an extended period of time at high doses, ensure that a multimodal approach to pain management, including mental health support (if needed), is in place prior to initiating an opioid analgesic taper [see Dosage and Administration (2.6),Warnings and Precautions (5.14)].

Infants born to mothers physically dependent on opioids will also be physically dependent and may exhibit respiratory difficulties and withdrawal signs [see Use In Specific Populations (8.1)].

10 OVERDOSAGE

Clinical Presentation

Acute overdose with morphine can be manifested by respiratory depression, somnolence progressing to stupor or coma, skeletal muscle flaccidity, cold and clammy skin, constricted pupils, and, in some cases, pulmonary edema, bradycardia, hypotension, hypoglycemia, partial or complete airway obstruction, atypical snoring, and death. Marked mydriasis rather than miosis may be seen with hypoxia in overdose situations [see Clinical Pharmacology (12.2)]. Toxic leukoencephalopathy has been reported after opioid overdose and can present hours, days, or weeks after apparent recovery from the initial intoxication.

Treatment of Overdose

In case of overdose, priorities are the re-establishment of a patent and protected airway and institution of assisted or controlled ventilation, if needed. Employ other supportive measures (including oxygen and vasopressors) in the management of circulatory shock and pulmonary edema as indicated. Cardiac arrest or arrhythmias will require advanced life support measures .

For clinically significant respiratory or circulatory depression secondary to opioid overdose, administer an opioid overdose reversal agent such as naloxone or nalmefene.

Because the duration of reversal would be expected to be less than the duration of action of morphine in MS CONTIN, carefully monitor the patient until spontaneous respiration is reliably reestablished. MS CONTIN will continue to release morphine and add to the morphine load for 24 to 48 hours or longer following ingestion, necessitating prolonged monitoring. If the response to an opioid overdose reversal agent is suboptimal or only brief in nature, administer additional reversal agent as directed by the product's prescribing information.

In an individual physically dependent on opioids, administration of the recommended usual dosage of the opioid overdose reversal agent will precipitate an acute withdrawal syndrome. The severity of the withdrawal symptoms experienced will depend on the degree of physical dependence and the dose of the reversal agent administered. If a decision is made to treat serious respiratory depression in the physically dependent patient, administration of the reversal agent should be initiated with care and by titration with smaller than usual doses of the reversal agent.

11 DESCRIPTION

MS CONTIN (morphine sulfate extended-release tablets) is for oral use and contains morphine sulfate, an opioid agonist.

Each tablet contains the following inactive ingredients common to all strengths: cetostearyl alcohol, hydroxyethyl cellulose, hypromellose, magnesium stearate, polyethylene glycol, talc, and titanium dioxide.

The tablet strengths describe the amount of morphine per tablet as the pentahydrated sulfate salt (morphine sulfate).

The 15 mg tablets also contain: FD&C Blue No. 2, lactose, polysorbate 80

The 30 mg tablets also contain: D&C Red No. 7, FD&C Blue No. 1, lactose, polysorbate 80

The 60 mg tablets also contain: D&C Red No. 30, D&C Yellow No. 10, hydroxypropyl cellulose, lactose

The 100 mg tablets also contain: black iron oxide

The 200 mg tablets also contain: D&C Yellow No. 10, FD&C Blue No. 1, hydroxypropyl cellulose

Morphine sulfate is an odorless, white, crystalline powder with a bitter taste. It has a solubility of 1 in 21 parts of water and 1 in 1000 parts of alcohol, but is practically insoluble in chloroform or ether. The octanol: water partition coefficient of morphine is 1.42 at physiologic pH and the pKb is 7.9 for the tertiary nitrogen (mostly ionized at pH 7.4). Its molecular weight is 758.83 and its structural formula is:

12 CLINICAL PHARMACOLOGY

12.1 Mechanism of Action

Morphine is a full opioid agonist and is relatively selective for the mu-opioid receptor, although it can bind to other opioid receptors at higher doses. The principal therapeutic action of morphine is analgesia. Like all full opioid agonists, there is no ceiling effect for analgesia with morphine.

Clinically, dosage is titrated to provide adequate analgesia and may be limited by adverse reactions, including respiratory and CNS depression.

The precise mechanism of the analgesic action is unknown. However, specific CNS opioid receptors for endogenous compounds with opioid-like activity have been identified throughout the brain and spinal cord and are thought to play a role in the analgesic effects of this drug.

12.2 Pharmacodynamics

CNS Depressant/Alcohol Interaction

Additive pharmacodynamic effects may be expected when MS CONTIN is used in conjunction with alcohol, other opioids, or illicit drugs that cause central nervous system depression.

Effects on the Central Nervous System

Morphine produces respiratory depression by direct action on brainstem respiratory centers. The respiratory depression involves a reduction in the responsiveness of the brainstem respiratory centers to both increases in carbon dioxide tension and electrical stimulation.

Morphine causes miosis, even in total darkness. Pinpoint pupils are a sign of narcotic overdose but are not pathognomonic (e.g., pontine lesions of hemorrhagic or ischemic origins may produce similar findings). Marked mydriasis rather than miosis may be seen with hypoxia in overdose situations.

Effects on the Gastrointestinal Tract and Other Smooth Muscle

Morphine causes a reduction in motility associated with an increase in smooth muscle tone in the antrum of the stomach and in the duodenum. Digestion of food in the small intestine is delayed and propulsive contractions are decreased. Propulsive peristaltic waves in the colon are decreased, while tone may be increased to the point of spasm, resulting in constipation. Other opioid-induced effects may include reduction in biliary and pancreatic secretions, spasm of the sphincter of Oddi, transient elevations in serum amylase, and opioid-induced esophageal dysfunction (OIED).

Effects on the Cardiovascular System

Morphine produces peripheral vasodilation which may result in orthostatic hypotension or syncope. Manifestations of histamine release and/or peripheral vasodilation may include pruritus, flushing, red eyes, sweating, and/or orthostatic hypotension.

Effects on the Endocrine System

Opioids inhibit the secretion of adrenocorticotropic hormone (ACTH), cortisol, and luteinizing hormone (LH) in humans [see Adverse Reactions (6.2)]. They also stimulate prolactin, growth hormone (GH) secretion, and pancreatic secretion of insulin and glucagon.

Use of opioids for an extended period of time may influence the hypothalamic-pituitary-gonadal axis, leading to androgen deficiency that may manifest as low libido, impotence, erectile dysfunction, amenorrhea, or infertility. The causal role of opioids in the clinical syndrome of hypogonadism is unknown because the various medical, physical, lifestyle, and psychological stressors that may influence gonadal hormone levels have not been adequately controlled for in studies conducted to date [see Adverse Reactions (6.2)].

Effects on the Immune System

Opioids have been shown to have a variety of effects on components of the immune system in in vitro and animal models. The clinical significance of these findings is unknown. Overall, the effects of opioids appear to be modestly immunosuppressive.

Concentration-Efficacy Relationships

The minimum effective analgesic concentration will vary widely among patients, especially among patients who have been previously treated with opioid agonists. The minimum effective analgesic concentration of morphine for any individual patient may increase over time due to an increase in pain, the development of a new pain syndrome, and/or the development of analgesic tolerance [see Dosage and Administration (2.1, 2.3)].

Concentration–Adverse Reaction Relationships

There is a relationship between increasing morphine plasma concentration and increasing frequency of dose-related opioid adverse reactions such as nausea, vomiting, CNS effects, and respiratory depression. In opioid-tolerant patients, the situation may be altered by the development of tolerance to opioid-related adverse reactions [see Dosage and Administration (2.1, 2.3, 2.4)].

12.3 Pharmacokinetics

Absorption

MS CONTIN is an extended-release tablet containing morphine sulfate. Morphine is released from MS CONTIN somewhat more slowly than from immediate-release oral preparations. Following oral administration of a given dose of morphine, the amount ultimately absorbed is essentially the same whether the source is MS CONTIN or an immediate-release formulation. Because of pre-systemic elimination (i.e., metabolism in the gut wall and liver) only about 40% of the administered dose reaches the central compartment.

The oral bioavailability of morphine is approximately 20 to 40%. When MS CONTIN is given on a fixed dosing regimen, steady-state is achieved in about a day.

Food Effect

The effect of food upon the systemic bioavailability of MS CONTIN has not been systematically evaluated for all strengths. One study, conducted with the 30 mg MS CONTIN tablets, showed no significant differences in Cmax and AUC(0-24h) values, whether the tablet was taken while fasting or with a high-fat breakfast.

Distribution

Once absorbed, morphine is distributed to skeletal muscle, kidneys, liver, intestinal tract, lungs, spleen, and brain. Morphine also crosses placental membranes and has been found in breast milk. The volume of distribution (Vd) for morphine is approximately 3 to 4 liters per kilogram and morphine is 30 to 35% reversibly bound to plasma proteins.

Elimination

Metabolism

The major pathways of morphine metabolism include glucuronidation to produce metabolites including morphine-3-glucuronide, M3G (about 50%) and morphine-6-glucuronide, M6G (about 5 to 15%) and sulfation in the liver to produce morphine-3-etheral sulfate. A small fraction (less than 5%) of morphine is demethylated. M6G has been shown to have analgesic activity but crosses the blood-brain barrier poorly, while M3G has no significant analgesic activity.

Excretion

The elimination of morphine occurs primarily as renal excretion of M3G and its effective half-life after intravenous administration is normally 2 to 4 hours. Approximately 10% of the dose is excreted unchanged in urine. In some studies involving longer periods of plasma sampling, a longer terminal half-life of about 15 hours was reported. A small amount of the glucuronide conjugate is excreted in the bile, and there is some minor enterohepatic recycling.

Specific Populations

Sex

A sex analysis of pharmacokinetic data from healthy subjects taking MS CONTIN indicated that morphine concentrations were similar in males and females.

Race/Ethnicity

Chinese subjects given intravenous morphine had a higher clearance when compared to Caucasian subjects (1852 +/- 116 ml/min compared to 1495 +/- 80 ml/min).

Hepatic Impairment

Morphine pharmacokinetics are altered in patients with cirrhosis. Clearance was found to decrease with a corresponding increase in half-life. The M3G and M6G to morphine plasma AUC ratios also decreased in these patients, indicating diminished metabolic activity. Adequate studies of the pharmacokinetics of morphine in patients with severe hepatic impairment have not been conducted.

Renal Impairment

Morphine pharmacokinetics are altered in patients with renal failure. The AUC is increased, and clearance is decreased and the metabolites, M3G and M6G, may accumulate to much higher plasma levels in patients with renal failure as compared to patients with normal renal function. Adequate studies of the pharmacokinetics of morphine in patients with severe renal impairment have not been conducted.

13 NONCLINICAL TOXICOLOGY

13.1 Carcinogenesis, Mutagenesis, Impairment of Fertility

Carcinogenesis

Long-term studies in animals to evaluate the carcinogenic potential of morphine have not been conducted.

Mutagenesis

No formal studies to assess the mutagenic potential of morphine have been conducted. In the published literature, morphine was found to be mutagenic in vitro increasing DNA fragmentation in human T-cells. Morphine was reported to be mutagenic in the in vivo mouse micronucleus assay and positive for the induction of chromosomal aberrations in mouse spermatids and murine lymphocytes. Mechanistic studies suggest that the in vivo clastogenic effects reported with morphine in mice may be related to increases in glucocorticoid levels produced by morphine in this species. In contrast to the above positive findings, in vitro studies in the literature have also shown that morphine did not induce chromosomal aberrations in human leukocytes or translocations or lethal mutations in Drosophila.

Impairment of Fertility

No formal nonclinical studies to assess the potential of morphine to impair fertility have been conducted. Several nonclinical studies from the literature have demonstrated adverse effects on male fertility in the rat from exposure to morphine. One study in which male rats were administered morphine sulfate subcutaneously prior to mating (up to 30 mg/kg twice daily) and during mating (20 mg/kg twice daily) with untreated females, a number of adverse reproductive effects including reduction in total pregnancies and higher incidence of pseudopregnancies at 20 mg/kg/day (3.2 times the HDD) were reported.

Studies from the literature have also reported changes in hormonal levels in male rats (i.e., testosterone, luteinizing hormone) following treatment with morphine at 10 mg/kg/day or greater (1.6 times the HDD).

Female rats that were administered morphine sulfate intraperitoneally prior to mating exhibited prolonged estrous cycles at 10 mg/kg/day (1.6 times the HDD).

Exposure of adolescent male rats to morphine has been associated with delayed sexual maturation and following mating to untreated females, smaller litters, increased pup mortality, and/or changes in reproductive endocrine status in adult male offspring have been reported (estimated 5 times the plasma levels at the HDD).

16 HOW SUPPLIED/STORAGE AND HANDLING

MS CONTIN® (morphine sulfate extended-release tablets) are supplied as follows:

15 mg - round, blue-colored, film-coated tablets bearing the symbol PF on one side and M 15 on the other.

Bottles (opaque plastic) of 100 tablets | NDC 42858-515-01

30 mg - round, lavender-colored, film-coated tablets bearing the symbol PF on one side and M 30 on the other.

Bottles (opaque plastic) of 100 tablets | NDC 42858-631-01

60 mg - round, orange-colored, film-coated tablets bearing the symbol PF on one side and M 60 on the other.

Bottles (opaque plastic) of 100 tablets | NDC 42858-760-01

100 mg - round, gray-colored, film-coated tablets bearing the symbol PF on one side and 100 on the other.

Bottles (opaque plastic) of 100 tablets | NDC 42858-799-01

200 mg - capsule-shaped, green-colored, film-coated tablets bearing the symbol PF on one side and M 200 on the other.

Bottles (opaque plastic) of 100 tablets | NDC 42858-900-01

STORAGE AND HANDLING

Store at 25°C (77°F); excursions permitted between 15° to 30°C (59° to 86°F) [see USP Controlled Room Temperature].

Store MS CONTIN securely and dispose of properly [see Patient Counseling Information (17)]. Dispense in a tight, light-resistant container.

17 PATIENT COUNSELING INFORMATION

Advise the patient to read the FDA-approved patient labeling (Medication Guide). Storage and Disposal

Because of the risks associated with accidental ingestion, misuse, and abuse, advise patients to store MS CONTIN securely, out of sight and reach of children, and in a location not accessible by others, including visitors to the home. Inform patients that leaving MS CONTIN unsecured can pose a deadly risk to others in the home [see Warnings and Precautions (5.1), Drug Abuse and Dependence (9.2)].

Advise patients and caregivers that when medicines are no longer needed, they should be disposed of promptly. Expired, unwanted, or unused MS CONTIN should be disposed of by flushing the unused medication down the toilet if a drug take-back option is not readily available. Inform patients that they can visit www.fda.gov/drugdisposal for a complete list of medicines recommended for disposal by flushing, as well as additional information on disposal of unused medicines.

Addiction, Abuse, and Misuse

Inform patients that the use of MS CONTIN, even when taken as recommended, can result in addiction, abuse, and misuse, which can lead to overdose and death [see Warnings and Precautions (5.1)]. Instruct patients not to share MS CONTIN with others and to take steps to protect MS CONTIN from theft or misuse.

Life-Threatening Respiratory Depression

Inform patients of the risk of life-threatening respiratory depression, including information that the risk is greatest when starting MS CONTIN or when the dosage is increased, and that it can occur even at recommended dosages.

Educate patients and caregivers on how to recognize respiratory depression and emphasize the importance of calling 911 or getting emergency medical help right away in the event of a known or suspected overdose [see Warnings and Precautions 5.2), Overdosage (10)].

Accidental Ingestion

Inform patients that accidental ingestion, especially by children, may result in respiratory depression or death [see Warnings and Precautions (5.2)].

Interactions with Benzodiazepines and Other CNS Depressants

Inform patients and caregivers that potentially fatal additive effects may occur if MS CONTIN is used with benzodiazepines or other CNS depressants, including alcohol (e.g., non-benzodiazepine sedative/hypnotics, anxiolytics, tranquilizers, muscle relaxants, general anesthetics, antipsychotics, gabapentinoids [gabapentin or pregabalin], and other opioids), and not to use these concomitantly unless supervised by a healthcare provider [see Warnings and Precautions (5.2), Drug Interactions (7)].

Patient Access to an Opioid Overdose Reversal Agent for the Emergency Treatment of Opioid Overdose

Inform patients and caregivers about opioid overdose reversal agents (e.g., naloxone, nalmefene). Discuss the importance of having access to an opioid overdose reversal agent, especially if the patient has risk factors for overdose (e.g., concomitant use of CNS depressants, a history of opioid use disorder, or prior opioid overdose) or if there are household members (including children) or other close contacts at risk for accidental ingestion or opioid overdose.

Discuss with the patient the options for obtaining an opioid overdose reversal agent (e.g., prescription, over-the-counter, or as part of a community-based program) [see Dosage and Administration (2.2), Warnings and Precautions (5.3)].

Educate patients and caregivers on how to recognize the signs and symptoms of an overdose.

Explain to patients and caregivers that effects of opioid overdose reversal agents like naloxone and nalmefene are temporary, and that they must call 911 or get emergency medical help right away in all cases of known or suspected opioid overdose, even if an opioid overdose reversal agent is administered [see Overdosage (10)].

Advise patients and caregivers:

- how to treat with the opioid overdose reversal agent in the event of an opioid overdose.
- to tell family and friends about their opioid overdose reversal agent, and to keep it in a place where family and friends can access it in an emergency.
- to read the Patient Information (or other educational material) that will come with their opioid overdose reversal agent. Emphasize the importance of doing this before an opioid emergency happens, so the patient and caregiver will know what to do.

Hyperalgesia and Allodynia

Inform patients and caregivers not to increase opioid dosage without first consulting a clinician. Advise patients to seek medical attention if they experience symptoms of hyperalgesia, including worsening pain, increased sensitivity to pain, or new pain [see Warnings and Precautions (5.6), Adverse Reactions (6.2)].

Serotonin Syndrome

Inform patients that opioids could cause a rare but potentially life-threatening condition called serotonin syndrome resulting from concomitant administration of serotonergic drugs. Warn patients of the symptoms of serotonin syndrome and to seek medical attention right away if symptoms develop. Instruct patients to inform their physicians if they are taking, or plan to take serotonergic medications [see Drug Interactions (7)].

MAOI Interaction

Inform patients not to take MS CONTIN while using any drugs that inhibit monoamine oxidase. Patients should not start MAOIs while taking MS CONTIN [see Warnings and Precautions (5.8), Drug Interactions (7)].

Important Administration Instructions

Instruct patients how to properly take MS CONTIN, including the following:

- Swallow MS CONTIN tablets whole [see Dosage and Administration (2.1)]
- Do not crush, chew, or dissolve the tablets [see Dosage and Administration (2.1)]
- Use MS CONTIN exactly as prescribed to reduce the risk of life-threatening adverse reactions (e.g., respiratory depression) [see Warnings and Precautions (5.2)]

Important Discontinuation Instructions

In order to avoid developing withdrawal symptoms, instruct patients not to discontinue MS CONTIN without first discussing a tapering plan with the prescriber [see Dosage and Administration (2.6)].

Driving or Operating Heavy Machinery

Inform patients that MS CONTIN may impair the ability to perform potentially hazardous activities such as driving a car or operating heavy machinery. Advise patients not to perform such tasks until they know how they will react to the medication [see Warnings and Precautions (5.15)].

Constipation

Advise patients of the potential for severe constipation, including management instructions and when to seek medical attention [see Adverse Reactions (6), Clinical Pharmacology (12.2)].

Adrenal Insufficiency

Inform patients that MS CONTIN could cause adrenal insufficiency, a potentially life-threatening condition. Adrenal insufficiency may present with non-specific symptoms and signs such as nausea, vomiting, anorexia, fatigue, weakness, dizziness, and low blood pressure. Advise patients to seek medical attention if they experience a constellation of these symptoms [see Warnings and Precautions (5.9)].

Hypotension

Inform patients that MS CONTIN may cause orthostatic hypotension and syncope. Instruct patients how to recognize symptoms of low blood pressure and how to reduce the risk of serious consequences should hypotension occur (e.g., sit or lie down, carefully rise from a sitting or lying position) [see Warnings and Precautions (5.10)].

Anaphylaxis

Inform patients that anaphylaxis has been reported with ingredients contained in MS CONTIN. Advise patients how to recognize such a reaction and when to seek medical attention [see Contraindications (4), Adverse Reactions (6)].

Pregnancy

Neonatal Opioid Withdrawal Syndrome

Inform female patients of reproductive potential that use of MS CONTIN for an extended period of time during pregnancy can result in neonatal opioid withdrawal syndrome, which may be life- threatening if not recognized and treated [see Warnings and Precautions (5.4), Use In Specific Populations (8.1)].

Embryo-Fetal Toxicity

Inform female patients of reproductive potential that MS CONTIN can cause fetal harm and to inform their healthcare provider of a known or suspected pregnancy [see Adverse Reactions (6.2)].

Lactation

Advise patients that breastfeeding is not recommended during treatment with MS CONTIN [see Use In Specific Populations (8.2)]

Infertility

Inform patients that chronic use of opioids may cause reduced fertility. It is not known whether these effects on fertility are reversible [see Use In Specific Populations (8.3)].

Healthcare professionals can telephone Rhodes Pharmaceuticals L.P.'s Medical Services Department (1-888-827-0616) for information on this product.

Manufactured by:
Purdue Pharma L.P.
Stamford, CT
06901-3431

Marketed by:
Rhodes Pharmaceuticals
Wilson, NC 27893

Medication Guide
MS CONTIN® (MS-KON-tin) (morphine sulfate extended-release tablets), CII

MS CONTIN is:

- A strong prescription pain medicine that contains an opioid (narcotic) that is used to manage severe and persistent pain that required an extended treatment period with a daily opioid pain medicine, when other pain medicines do not treat your pain well enough or you cannot tolerate them.
- A long-acting (extended-release) opioid pain medicine that can put you at risk for overdose and death. Even if you take your dose correctly as prescribed you are at risk for opioid addiction, abuse, and misuse that can lead to death.
- Not to be taken on an "as needed" basis.

Important information about MS CONTIN:

- Get emergency help or call 911 right away if you take too much MS CONTIN (overdose). When you first start taking MS CONTIN, when your dose is changed, or if you take too much (overdose), serious or life-threatening breathing problems that can lead to death may occur. Ask your healthcare provider about medicines like naloxone or nalmefene that can be used in an emergency to reverse an opioid overdose.
- Taking MS CONTIN with other opioid medicines, benzodiazepines, gabapentinoids (gabapentin or pregabalin), alcohol, or other central nervous system depressants (including street drugs) can cause severe drowsiness, decreased awareness, breathing problems, coma, and death.
- Never give anyone else your MS CONTIN. They could die from taking it. Selling or giving away MS CONTIN is against the law.
- Store MS CONTIN securely, out of sight and reach of children, and in a location not accessible by others, including visitors to the home.

Do not take MS CONTIN if you have:

- severe asthma, trouble breathing, or other lung problems.
- a bowel blockage or have narrowing of the stomach or intestines.

Before taking MS CONTIN, tell your healthcare provider if you have a history of:

- head injury, seizures
- problems urinating

- liver, kidney, thyroid problems
- pancreas or gallbladder problems

- abuse of street or prescription drugs, alcohol addiction, opioid overdose, or mental health problems.

Tell your healthcare provider if you are:

- Noticing your pain getting worse. If your pain gets worse after you take MS CONTIN, do not take more of MS CONTIN without first talking to your healthcare provider. Talk to your healthcare provider if the pain you have increases, if you feel more sensitive to pain, or if you have new pain after taking MS CONTIN.
- Pregnant or planning to become pregnant. Use of MS CONTIN for an extended period of time during pregnancy can cause withdrawal symptoms in your newborn baby that could be life- threatening if not recognized and treated.
- Breastfeeding. Not recommended during treatment with MS CONTIN. It may harm your baby.
- Living in a household where there are small children or someone who has abused street or prescription drugs.
- Taking prescription or over-the-counter medicines, vitamins, or herbal supplements. Taking MS CONTIN with certain other medicines can cause serious side effects.

When taking MS CONTIN:

- Do not change your dose. Take MS CONTIN exactly as prescribed by your healthcare provider. Use the lowest dose possible for the shortest duration.
- Take your prescribed dose every 8 to 12 hours, as directed by your healthcare provider. Do not take more than your prescribed dose. If you miss a dose, take your next dose at the usual time.
- Swallow MS CONTIN whole. Do not cut, break, chew, crush, dissolve, snort, or inject MS CONTIN because this may cause you to overdose and die.
- Call your healthcare provider if the dose you are taking does not control your pain.
- Do not stop taking MS CONTIN without talking to your healthcare provider.
- Dispose of expired, unwanted, or unused MS CONTIN by promptly flushing down the
  toilet, if a drug take-back option is not readily available. Visit www.fda.gov/drugdisposal for additional information on disposal of unused medicines.

While taking MS CONTIN DO NOT:

- Drive or operate heavy machinery, until you know how MS CONTIN affects you. MS CONTIN can make you sleepy, dizzy, or lightheaded.

- Drink alcohol or use prescription or over-the-counter medicines that contain alcohol. Using products containing alcohol during treatment with MS CONTIN may cause you to overdose and die.

The possible side effects of MS CONTIN are:

- Constipation, nausea, sleepiness, vomiting, tiredness, headache, dizziness, abdominal pain. Call your healthcare provider if you have any of these symptoms and they are severe.

Get emergency medical help or call 911 right away if you have:

- trouble breathing, shortness of breath, fast heartbeat, chest pain, swelling of your face, tongue, or throat, extreme drowsiness, light-headedness when changing positions, feeling faint, agitation, high body temperature, trouble walking, stiff muscles, or mental changes such as confusion.

These are not all the possible side effects of MS CONTIN. Call your healthcare provider for medical advice about side effects. You may report side effects to FDA at 1-800-FDA-1088. For more information, go to dailymed.nlm.nih.gov.
Manufactured by: Purdue Pharma L.P., Stamford, CT 06901-3431,
www.purduepharma.com or call 1-888-726-7535
Marketed by: Rhodes Pharmaceuticals, Wilson, NC 27893 US, http://rhodespharma.com, or call 1-888-827-0616.

This Medication Guide has been approved by the U.S. Food and Drug Administration.

Revised: 12/2025

MS Contin® CII
(morphine sulfate extended-release tablets)

PRINCIPAL DISPLAY PANEL - 15 mg Tablet Bottle Label

Attention Dispenser: Accompanying
Medication Guide must be provided to
the patient upon dispensing.

NDC 42858-515-01

MS Contin®
(morphine sulfate
extended-release tablets)

CII

15 mg

Rhodes

Rx Only

100 Tablets

PRINCIPAL DISPLAY PANEL - 30 mg Tablet Bottle Label

Attention Dispenser: Accompanying
Medication Guide must be provided to
the patient upon dispensing.

NDC 42858-631-01

MS Contin®
(morphine sulfate
extended-release tablets)

CII

30 mg

Rhodes

Rx Only

100 Tablets

PRINCIPAL DISPLAY PANEL - 60 mg Tablet Bottle Label

Attention Dispenser: Accompanying
Medication Guide must be provided to
the patient upon dispensing.

NDC 42858-760-01

MS Contin®
(morphine sulfate
extended-release tablets)

CII

60 mg

Rhodes

Rx Only

100 Tablets

PRINCIPAL DISPLAY PANEL - 100 mg Tablet Bottle Label

Attention Dispenser: Accompanying
Medication Guide must be provided to
the patient upon dispensing.

NDC 42858-799-01

MS Contin®
(morphine sulfate
extended-release tablets)

CII

100 mg

Rhodes

Rx Only
100 Tablets

for use in opioid-
tolerant patients
only

PRINCIPAL DISPLAY PANEL - 200 mg Tablet Bottle Label

Attention Dispenser: Accompanying
Medication Guide must be provided to
the patient upon dispensing.

NDC 42858-900-01

MS Contin®
(morphine sulfate
extended-release tablets)

CII

200 mg

Rhodes

Rx Only
100 Tablets

for use in opioid-
tolerant patients
only